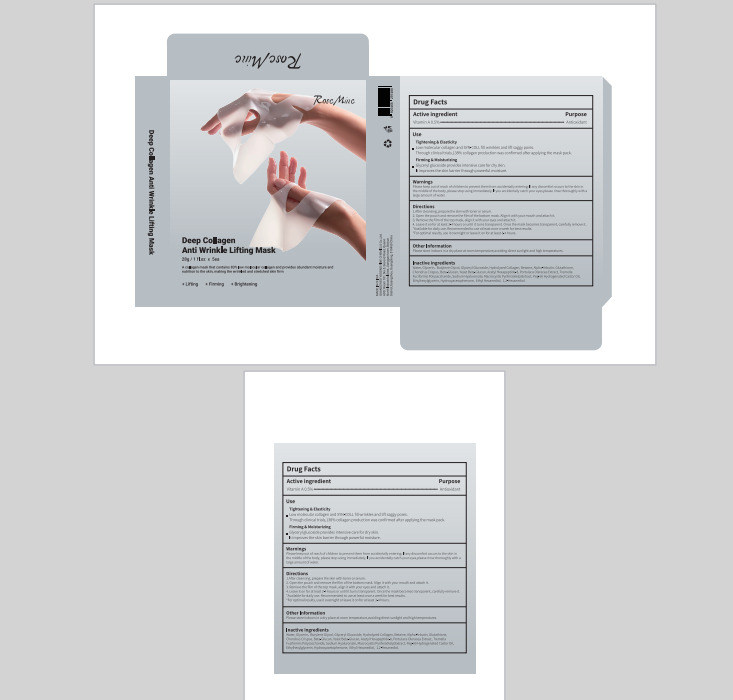 DRUG LABEL: RoseMine Deep Collagen Anti Wrinkle Lifting Mask
NDC: 84558-002 | Form: CLOTH
Manufacturer: GUANGZHOU YUSONG FINE CHEMICLS Co., Ltd
Category: otc | Type: HUMAN OTC DRUG LABEL
Date: 20241007

ACTIVE INGREDIENTS: VITAMIN A 0.5 g/100 g
INACTIVE INGREDIENTS: ACETYL HEXAPEPTIDE-8; GLUTATHIONE; CHONDRUS CRISPUS; PURSLANE; HYALURONATE SODIUM; PEG-60 HYDROGENATED CASTOR OIL; ETHYLHEXYLGLYCERIN; HYDROXYACETOPHENONE; ETHOHEXADIOL; 1,2-HEXANEDIOL; BETAINE; GLYCERYL GLUCOSIDE; BUTYLENE GLYCOL; GLYCERIN; ALPHA-ARBUTIN; WATER

84558-002

Active Ingredient(s)

Vitamin A 0.5%

Purpose

Antioxidant

Use

Tightening & Elasticity

1.Low molecular collagen and SYN-COLL fill wrinkles and lift saggy pores.
Through clinical trials,138% collagen production was confirmed after applying the mask pack.
Firming & Moisturizing
1.Glyceryl glucoside provides intensive care for dry skin.
It improves the skin barrier through powerful moisture.

Warnings

Please keep out of reach of children to prevent them from accidentally entering; If any discomfort occurs to the skin in
the middle of the body, please stop using immediately; If you accidentally catch your eyes,please rinse thoroughly with a
large amount of water.

Do not use

History of allergies or allergic reaction to any ingredient in this product.

WHEN USING

If you accidentally catch your eyes,please rinse thoroughly witha large amount of water.

STOP USE

If there are any adverse reactions or discomfort, please stop using

KEEP OUT OF REACH OF CHILDREN

Please keep out of reach of children, Prevent accidental entry

Directions

1.After cleansing. prepare the skin with toner or serum.
2. Open the pouch and remove the film of the bottom mask. Align it with your mouth and attach it.
3. Remove the film of the top mask, align it with your eyes and attach it.
4. Leave it on for at least 3-4 hours or until it turns transparent. Once the mask becomes transparent, carefully remove it.
*Available for daily use. Recommended to use at least once a week for best results.
*For optimal results, use it overnight or leave it on for at least 3-4 hours.

Other information

Please store indoors in a dry place at room temperature ,avoiding direct sunlight and high temperatures.

Inactive ingredients

Water, Glycerin, Butylene Glycol, Glyceryl Glucoside, Hydrolyzed Collagen, Betaine, Alpha-Arbutin, Glutathione,
Chondrus Crispus, Beta-Glucan, Yeast Beta-Glucan, Acetyl Hexapeptide-8, Portulaca Oleracea Extract, Tremella
Fucifrmis Polysaccharide, Sodium Hyaluronate, Macrocystis Pyrifera(Kelp)Extract, Peg- 60 Hydrogenated Castor Oil,
Ethy.hexylglycerin, Hydroxyacetophenone, Ethyl Hexanediol, 1,2-Hexanediol.